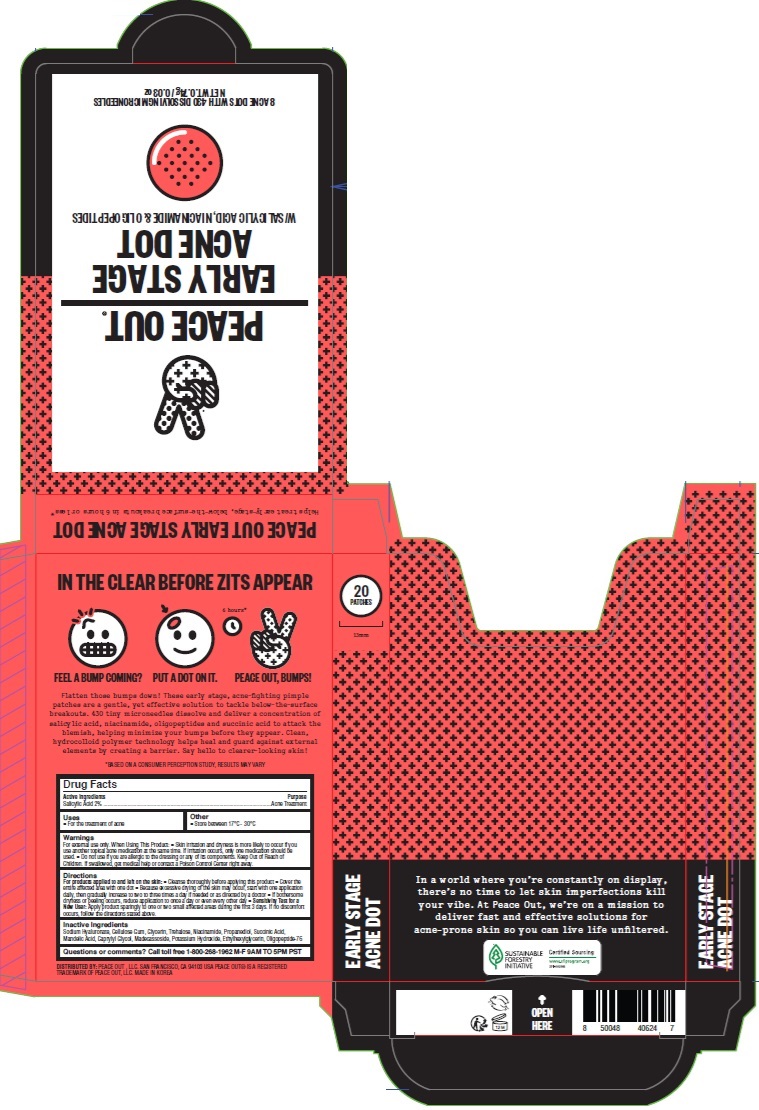 DRUG LABEL: Peace Out Early Stage Acne Dot
NDC: 71494-007 | Form: PATCH
Manufacturer: Peace Out LLC.
Category: otc | Type: HUMAN OTC DRUG LABEL
Date: 20240620

ACTIVE INGREDIENTS: SALICYLIC ACID 0.14 mg/1 1
INACTIVE INGREDIENTS: POTASSIUM HYDROXIDE; ETHYLHEXYLGLYCERIN; NIACINAMIDE; MADECASSOSIDE; SUCCINIC ACID; GLYCERIN; PROPANEDIOL; TREHALOSE; HYALURONATE SODIUM; MANDELIC ACID; CAPRYLYL GLYCOL; CARBOXYMETHYLCELLULOSE SODIUM, UNSPECIFIED FORM

Peace Out Early Stage Acne Dot

Active Ingredients

Salicylic Acid 2%

Purpose

Acne Treatment

Uses

- For the treatment of acne

Warnings

For external use only. When Using This Product

- Skin irritation and dryness is more likely to occur if you use another topical acne medication at the same time. If irritation occurs, only one medication should be used.
- Do not use if you are allergic to the dressing or any of its components.

Keep Out of Reach of Children.

If swallowed, get medical help or contact a Posion Control Center right away.

Directions

For products applied to and left on the skin:

- Cleanse thoroughly before applying this product
- Because excessive drying of the skin may occur, start with on application daily, then gradually increase to two to three times a day if needed or as directed by a doctor
- If bothersome dryness or peeling occurs, reduce application to once a day or even every other day
- Sensitivity Test for a New User. Apply product sparingly to one or two small affected areas during the first 3 days. If no discomfort occurs, follow the directions stated above.

Inactive Ingredients

Sodium Hyaluronate, Cellulose Gum, Glycerin, Trehalose, Niacinamide, Propanediol, Succinic Acid, Mandelic Acid, Caprylyl Glycol, Madecassoside, Potassium Hydroxide, Ethylhexylglycerin, Oligopeptide-76

Questions or comments?

Call toll free 1-800-268-1962 M-F 9AM TO 5PM PST

Other

- Store between 17ºC - 30ºC